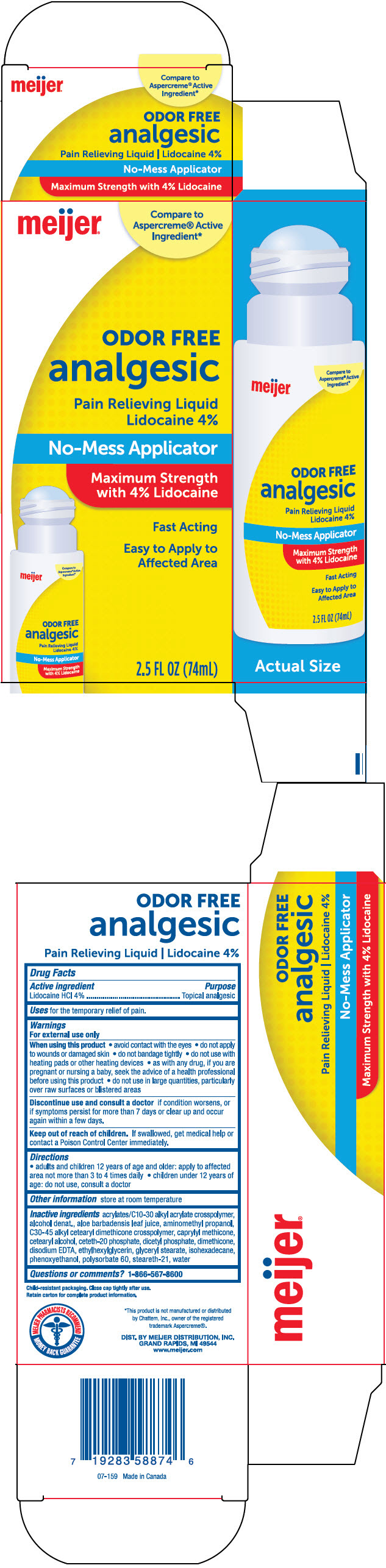 DRUG LABEL: Meijer Odor Free Analgesic Pain Relieving
NDC: 41250-351 | Form: LIQUID
Manufacturer: Meijer Distribution, Inc
Category: otc | Type: HUMAN OTC DRUG LABEL
Date: 20250114

ACTIVE INGREDIENTS: LIDOCAINE HYDROCHLORIDE 40 mg/1 mL
INACTIVE INGREDIENTS: CARBOMER INTERPOLYMER TYPE A (ALLYL SUCROSE CROSSLINKED); Alcohol; Aloe Vera Leaf; Aminomethylpropanol; Caprylyl Trisiloxane; Cetostearyl Alcohol; Ceteth-20 Phosphate; Dihexadecyl Phosphate; Dimethicone; Edetate Disodium; Ethylhexylglycerin; Glyceryl Monostearate; Isohexadecane; Phenoxyethanol; Polysorbate 60; Steareth-21; Water

Meijer® Odor Free Analgesic Pain Relieving Liquid
Topical Analgesic

Drug Facts

Active ingredient

Lidocaine HCl 4%

Purpose

Topical analgesic

Uses

for the temporary relief of pain.

Warnings

For external use only

When using this product

- avoid contact with eyes
- do not apply to wounds or damaged skin
- do not bandage tightly
- do not use with heating pads or other heating devices
- as with any drug, if you are pregnant or nursing a baby, seek the advice of a health professional before using this product
- do not use in large quantities, particularly over raw surfaces or blistered areas

STOP USE

Discontinue use and consult a doctor if condition worsens, or if symptoms persist for more than 7 days or clear up and occur again within a few days.

Keep out of reach of children. If swallowed, get medical help or contact a Poison Control Center immediately.

Directions

- adults and children 12 years of age and older: apply to affected area not more than 3 to 4 times daily
- children under 12 years of age: do not use, consult a doctor

Other information

store at room temperature

Inactive ingredients

Acrylates/C10-30 Alkyl Acrylate Crosspolymer, Alcohol denat., Aloe Barbadensis Leaf Juice, Aminomethyl Propanol, C30-45 Alkyl Cetearyl Dimethicone Crosspolymer, Caprylyl Methicone, Cetearyl Alcohol, Ceteth-20 Phosphate, Dicetyl Phosphate, Dimethicone, Disodium EDTA, Ethylhexylglycerin, Glyceryl Stearate, Isodexadecane, Phenoxyethanol, Polysorbate 60, Steareth-21, Water.

Questions or comments?

1-866-567-8600

DIST. BY MEIJER DISTRIBUTION, INC.
GRAND RAPIDS, MI 49544

PRINCIPAL DISPLAY PANEL - 74 mL Cylinder Carton

meijer®

Compare to
Aspercreme® Active
Ingredient*

ODOR FREE
analgesic

Pain Relieving Liquid
Lidocaine 4%

No-Mess Applicator

Maximum Strength
with 4% Lidocaine

Fast Acting

Easy to Apply to
Affected Area

2.5 FL OZ (74mL)